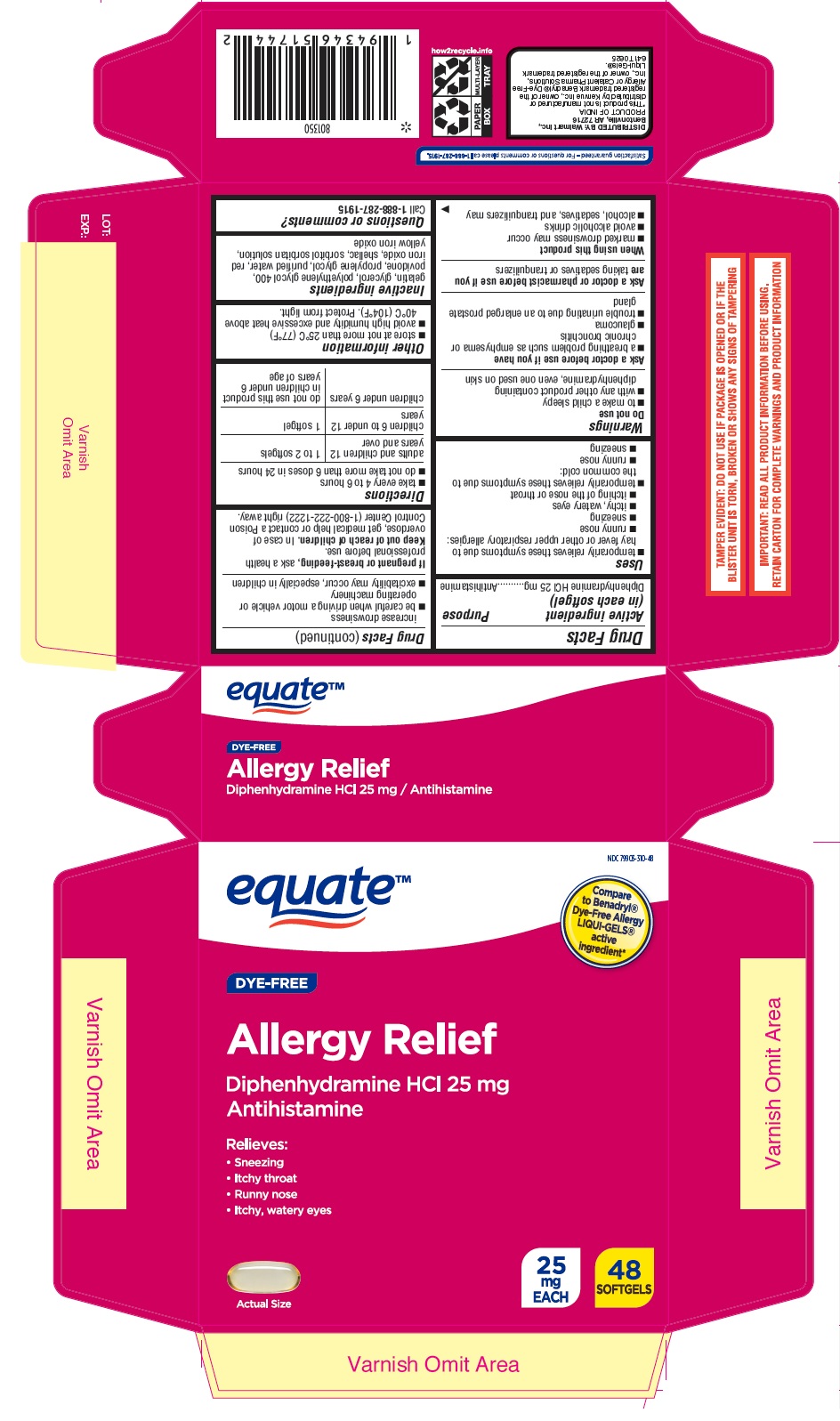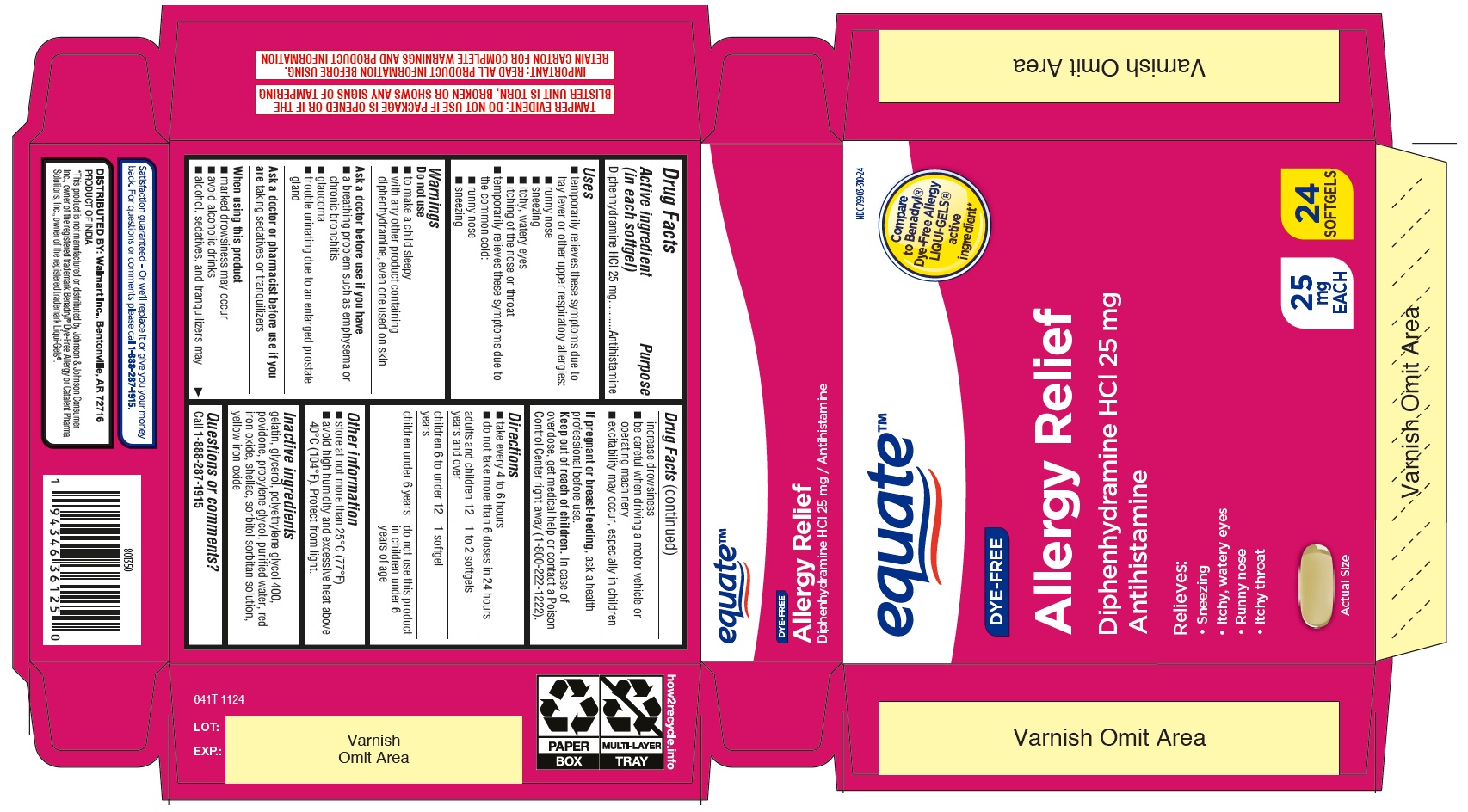 DRUG LABEL: Allergy Relief
NDC: 79903-310 | Form: CAPSULE, LIQUID FILLED
Manufacturer: Walmart Inc.
Category: otc | Type: HUMAN OTC DRUG LABEL
Date: 20250625

ACTIVE INGREDIENTS: DIPHENHYDRAMINE HYDROCHLORIDE 25 mg/1 1
INACTIVE INGREDIENTS: SHELLAC; FERRIC OXIDE YELLOW; GLYCERIN; POVIDONE; PROPYLENE GLYCOL; WATER; GELATIN; FERRIC OXIDE RED; SORBITOL SOLUTION; SORBITAN; POLYETHYLENE GLYCOL 400

Walmart Diphenhydramine Hydrochloride 25 mg Softgels

Active ingredient (in each softgel)

Diphenhydramine HCl 25 mg

Purpose

Antihistamine

Uses

temporarily relieves these symptoms due to hay fever or other upper respiratory allergies:

- runny nose
- sneezing
- itchy, watery eyes
- itching of the nose or throat

temporarily relieves these symptoms due to the common cold:

- runny nose
- sneezing

Warnings

Do not use

- to make a child sleepy
- with any other product containing diphenhydramine, even one used on skin

Ask a doctor before use if you have

- a breathing problem such as emphysema or chronic bronchitis
- glaucoma
- trouble urinating due to enlarged prostate gland

Ask a doctor or pharmacist before use if you are

taking sedatives or tranquilizers

When using this product

- marked drowsiness may occur
- avoid alcoholic drinks
- alcohol, sedatives, and tranquilizers may increase drowsiness
- be careful when driving a motor vehicle or operating machinery
- excitability may occur, especially in children

If pregnant or breast-feeding,

ask a health professional before use.

Keep out of reach of children.

In case of overdose, get medical help or contact a Poison Control Center right away (1-800-222-1222).

Directions

take every 4 to 6 hours

do not take more than 6 doses in 24 hours

adults and children 12 years and over: 1 to 2 softgels

children 6 to under 12 years: 1 softgel

children under 6 years: do not use this product in children under 6 years of age

Other information

- store at not more than 25°C (77° F)
- avoid high humidity and excessive heat above 40°C (104°F). Protect from light.

INACTIVE INGREDIENT

Inactive ingredients gelatin, glycerol, polyethylene glycol 400, povidone, propylene glycol, purified water, red iron oxide, shellac, sorbitol sorbitan solution, yellow iron oxide

Questions or comments?

Call 1-888-287-1915